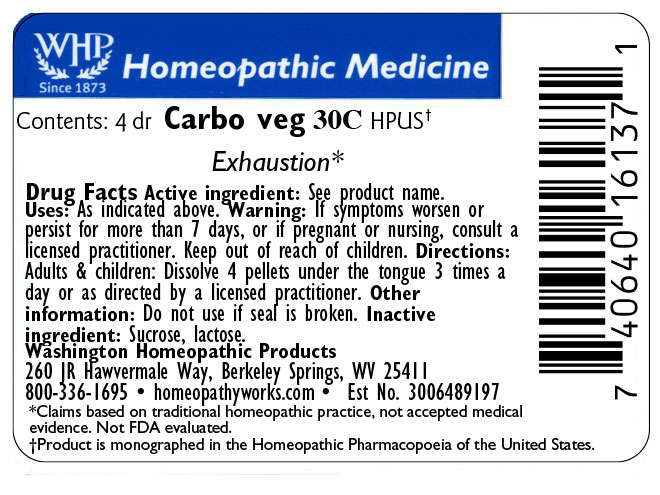 DRUG LABEL: Carbo vegetabilis
NDC: 71919-825 | Form: PELLET
Manufacturer: Washington Homeopathic Products
Category: homeopathic | Type: HUMAN OTC DRUG LABEL
Date: 20250218

ACTIVE INGREDIENTS: ACTIVATED CHARCOAL 30 [hp_C]/1 1
INACTIVE INGREDIENTS: SUCROSE; LACTOSE

ACTIVE INGREDIENT

ACTIVATED CHARCOAL (Carbo veg)

PURPOSE

Indicated for Exhaustion

KEEP OUT OF REACH OF CHILDREN

As with all medicines, keep out of reach of children.

INDICATIONS AND USAGE

Carbo Veg Exhaustion

WARNINGS

If symptoms worsen or persist for more than 7 days, or if pregnant or nursing, consult a licensed practitioner.

INACTIVE INGREDIENT

SUCROSE/LACTOSE

DOSAGE AND ADMINISTRATION

Directions: Adults & children: Dissolve 4 pellets under the tongue 3 times a day or as directed by a licensed practitioner. Other information: Do not use if seal is broken.

PACKAGE LABEL

The OTC potency range of Carbo veg is 30C - 200C.

Availability is subject to change.